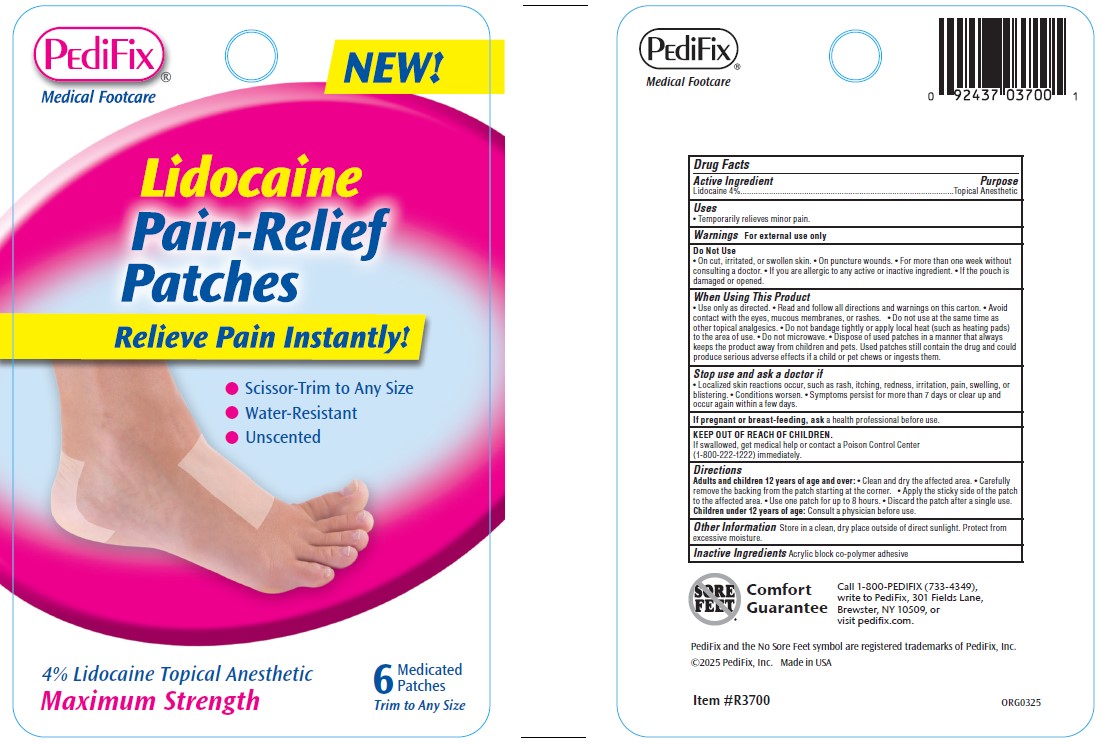 DRUG LABEL: PediFix Lidocaine Pain-Relief Patches
NDC: 68927-3700 | Form: PATCH
Manufacturer: PediFix, Inc
Category: otc | Type: HUMAN OTC DRUG LABEL
Date: 20250505

ACTIVE INGREDIENTS: LIDOCAINE 4 mg/100 mg
INACTIVE INGREDIENTS: POLYQUATERNIUM-7 49.6 mg/100 mg

DRUG FACTS

ACTIVE INGREDIENT

lIDOCAINE 4%

PURPOSE

Topical Anesthetic

INDICATIONS AND USAGE

Temporarily relieves minor pain

WARNINGS

For external use only

DO NOT USE

• On cut, irritated, or swollen skin. • On puncture wounds. • For more than one week without
consulting a doctor. • If you are allergic to any active or inactive ingredient. • If the pouch is
damaged or opened.

WHEN USING

- Use only as directed.
- Read and follow all directions and warnings on this carton.
- Avoid contact with the eyes, mucous membranes, or rashes.
- Do not use at the same time as other topical analgesics.
- Do not bandage tightly or apply local heat (such as heating pads) to the area of use.
- Do not microwave.
- Dispose of used patches in a manner that always keeps the product away from children and pets. Used patches still contain the drug and could produce serious adverse effects if a child or pet chews or ingests them.

STOP USE

- Localized skin reactions occur, such as rash, itching, redness, irritation, pain, swelling, or blistering.
- Conditions worsen.
- Symptoms persist for more than 7 days or clear up and occur again within a few days.

PREGNANCY OR BREAST FEEDING

ask a health professional before use.

KEEP OUT OF REACH OF CHILDREN

If swallowed, get medical help or contact a Poison Control Center
(1-800-222-1222) immediately.

DOSAGE AND ADMINISTRATION

Adults and children 12 years of age and over:

- Clean and dry the affected area.
- Carefully remove the backing from the patch starting at the corner.
- Apply the sticky side of the patch to the affected area.
- Use one patch for up to 8 hours.
- Discard the patch after a single use.

Children under 12 years of age: Consult a physician before use.

OTHER SAFETY INFORMATION

Store in a clean, dry place outside of direct sunlight. Protect from excessive moisture.

INACTIVE INGREDIENT

Acrylic block co-polymer adhesive

Call 1-800-PEDIFIX (733-4349),
write to PediFix, 301 Fields Lane,
Brewster, NY 10509, or
visit pedifix.com.

PACKAGE LABEL

PediFix

Meidcal Footcare

Lidocain

Pain-Relief

Patches

Relieve Pain Instantly!

Scissor-Trim to Any Size

Water-Resistant

Unscented

4% Lidocaine Topical Anesthetic

Maximum Strength

6

Medicated Patches

Trim to Any Size